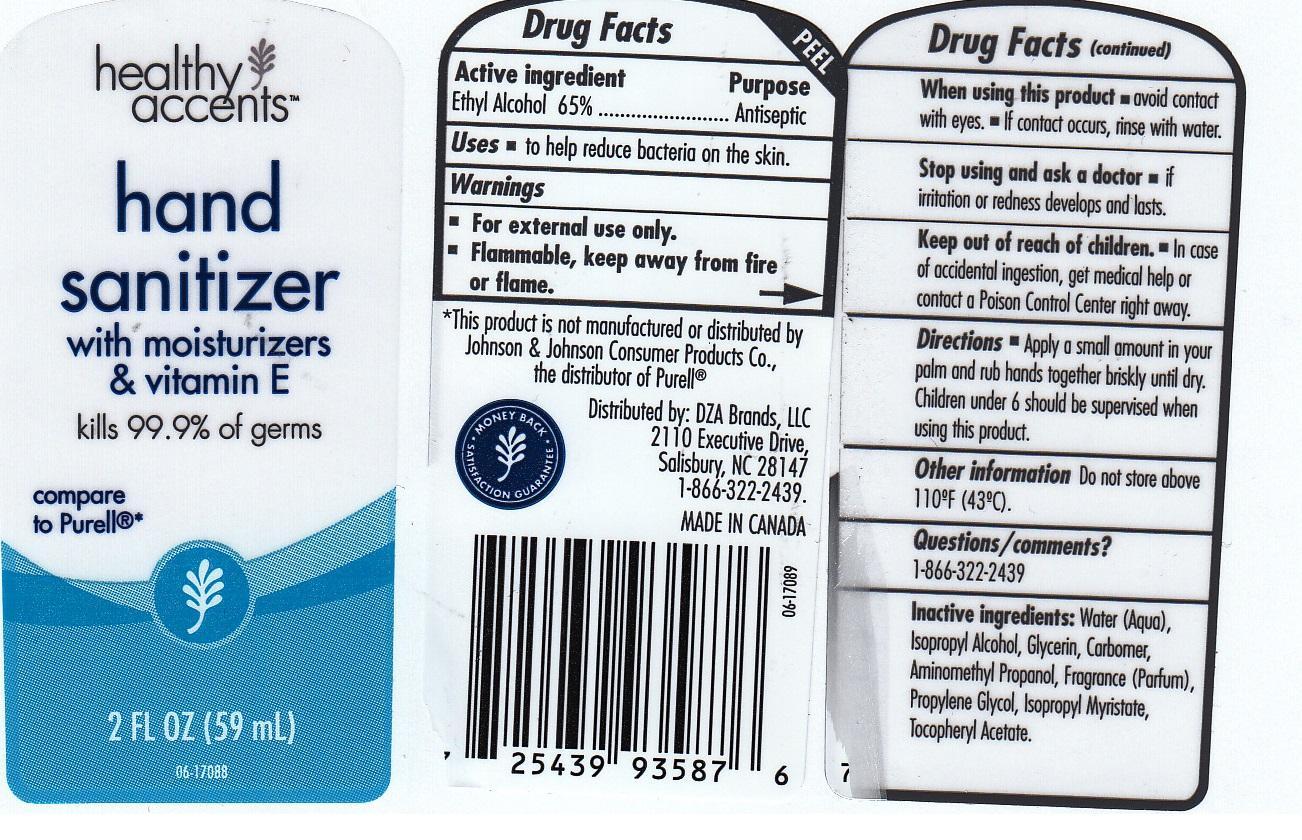 DRUG LABEL: HAND SANITIZER
NDC: 55316-253 | Form: GEL
Manufacturer: DZA BRANDS LLC
Category: otc | Type: HUMAN OTC DRUG LABEL
Date: 20130529

ACTIVE INGREDIENTS: ALCOHOL 650 mg/1 mL
INACTIVE INGREDIENTS: WATER; ISOPROPYL ALCOHOL; GLYCERIN; CARBOMER 934; AMINOMETHYLPROPANOL; PROPYLENE GLYCOL; ISOPROPYL MYRISTATE; .ALPHA.-TOCOPHEROL ACETATE, D-

DRUG FACTS

ACTIVE INGREDIENT

ETHYL ALCOHOL 65%

PURPOSE

ANTISEPTIC

USES

TO HELP REDUCE BACTERIA ON THE SKIN.

OTHER INFORMATION

FOR EXTERNAL USE ONLY. FLAMMABLE, KEEP AWAY FROM FIRE OR FLAME.

WHEN USING THIS PRODUCT

AVOID CONTACT WITH EYES. IF CONTACT OCCURS, RINSE WITH WATER.

STOP USING AND ASK A DOCTOR

IF IRRITATION OR REDNESS DEVELOPS AND LASTS.

KEEP OUT OF REACH OF CHILDREN

IN CASE OF ACCIDENTAL INGESTION, GET MEDICAL HELP OR CONTACT A POISON CONTROL CENTER RIGHT AWAY.

DOSAGE AND ADMINISTRATION

APPLY A SMALL AMOUNT IN YOUR PALM AND RUB HANDS TOGETHER BRISKLY UNTIL DRY. CHILDREN UNDER 6 SHOULD BE SUPERVISED WHEN USING THIS PRODUCT.

OTHER INFORMATION

STORE AT A TEMPERATURE BELOW 110 FAHRENHEIT (43 DEGREES CELCIUS).

QUESTIONS AND COMMENTS

1-866-322-2439

INACTIVE INGREDIENTS

WATER, ISOPROPYL ALCOHOL, GLYCERIN, CARBOMER, AMINOMETHYL PROPANOL, FRAGRANCE, PROPYLENE GLYCOL, ISOPROPYL MYRISTATE, TOCOPHERYL ACETATE.